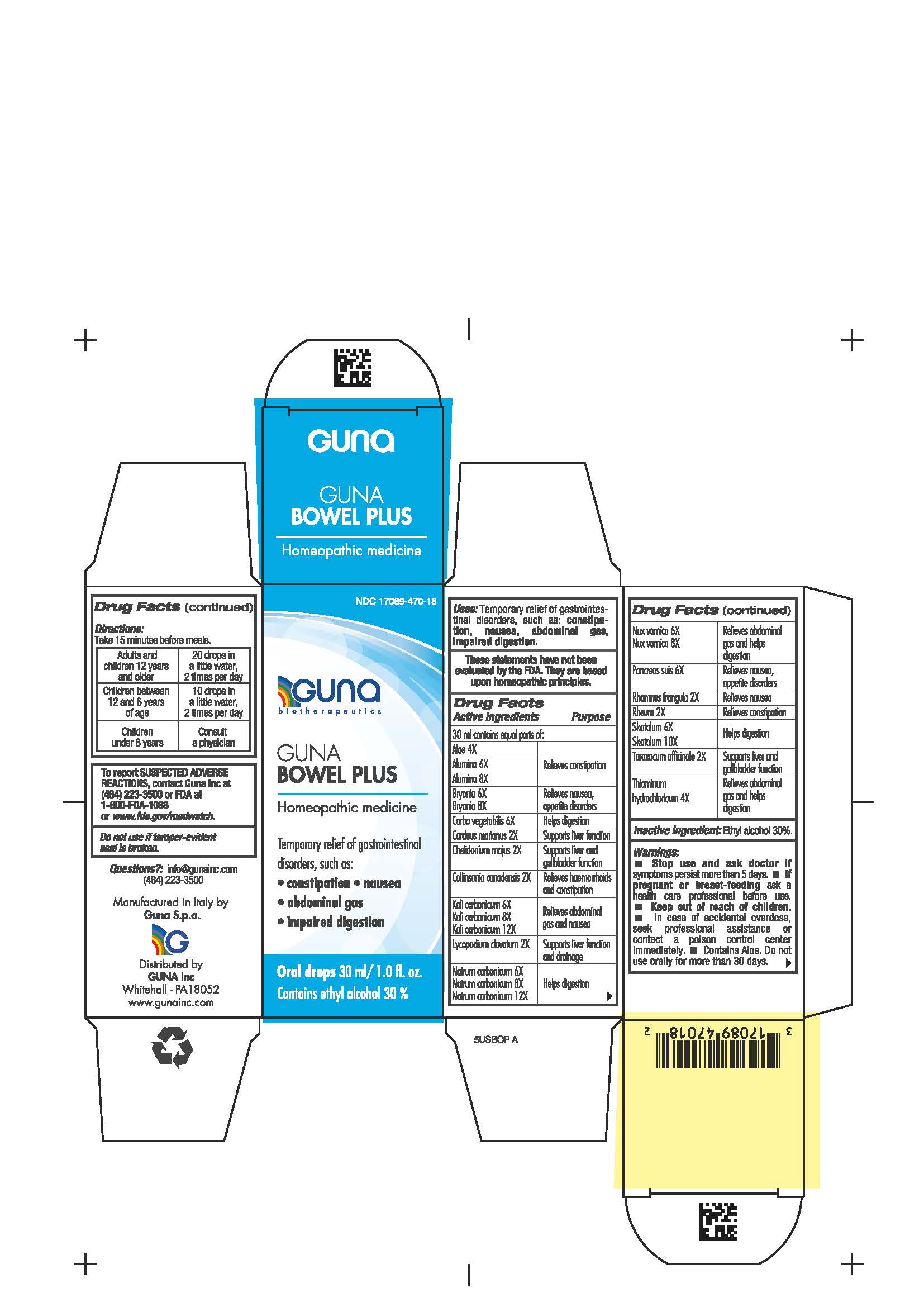 DRUG LABEL: GUNA BOWEL PLUS
NDC: 17089-470 | Form: SOLUTION/ DROPS
Manufacturer: Guna spa
Category: homeopathic | Type: HUMAN OTC DRUG LABEL
Date: 20210117

ACTIVE INGREDIENTS: ALOE 4 [hp_X]/30 mL; ALUMINUM OXIDE 6 [hp_X]/30 mL; BRYONIA ALBA ROOT 6 [hp_X]/30 mL; SILYBUM MARIANUM SEED 2 [hp_X]/30 mL; CHELIDONIUM MAJUS 2 [hp_X]/30 mL; ACTIVATED CHARCOAL 6 [hp_X]/30 mL; COLLINSONIA 2 [hp_X]/30 mL; SUS SCROFA PANCREAS 6 [hp_X]/30 mL; POTASSIUM CARBONATE 6 [hp_X]/30 mL; SODIUM CARBONATE 6 [hp_X]/30 mL; LYCOPODIUM CLAVATUM SPORE 2 [hp_X]/30 mL; STRYCHNOS NUX-VOMICA SEED 6 [hp_X]/30 mL; FRANGULA ALNUS BARK 2 [hp_X]/30 mL; RHUBARB 2 [hp_X]/30 mL; SKATOLE 6 [hp_X]/30 mL; TARAXACUM OFFICINALE 2 [hp_X]/30 mL; THIAMINE 4 [hp_X]/30 mL
INACTIVE INGREDIENTS: ALCOHOL 9 mL/30 mL

GUNA BOWEL PLUS

INDICATIONS AND USAGE

Take 15 minutes before meals

Inactive ingredient: Ethyl alcohol 30%

QUESTIONS

Questions?: info@gunainc.com, tel. (484) 223-3500

DIRECTIONS

Adults and children 12 years and older 20 drops in a little water, 2 times per day
Children between 12 years and 6 years of age 10 drops in a little water, 2 times per day
Children under 6 years: consulta a physician

WARNINGS

Keep out of reach of children

PREGNANCY

If pregnant or breast-feeding ask a health care professional before use

WARNINGS

- Stop use and ask doctor if symptoms persist more than 5 days.
- If pregnant or breast-feeding ask a health care professional before use.
- Keep out of reach of children. In case of accidental overdose, seek professional assitance ot or contact a Poison Control Center immediately
- Contains Aloe: do not use orally for more than 30 days.
- Contains ethyl alcohol 30%

USES

Temporary relief of gastrointestinal disorders, such as:

- constipation
- nausea
- abdominal gas
- impaired digestion

ACTIVE INGREDIENTS/PURPOSE

Aloe 4X Relieves constipation

Alumina 6X, 8X Relieves constipation

Bryonia 6X, 8X Relieves nausea, appetite disorders

Carbo vegetabilis 6X Helps digestion

Carduus marianus 2X Supports liver function

Chelidonium majus 2X Supports liver and gallbladder function

Collinsonia canadensis 2X Relieves hemorrhoids and constipation

Kali carbonicum 6X, 8X, 12X Relieves abdominal gas and nausea

Lycopodium clavatum 2X Supports liver function and drainage

Natrum carbonicum 6X, 8X, 12X Helps digestion

Nux vomica 6X, 8X Relieves abdominal gas and helps digestion

Pancreas suis 6X Relieves nausea, appetite disorders

Rhamnus frangula 2X Relieves nausea

Rheum 2X Relieves constipation

Skatolum 6X, 10X Helps digestion

Taraxacum officinale 2X Supports liver and gallbladder function

Thiaminum hydroc. 4X Relieves abdominal gas and helps digestion